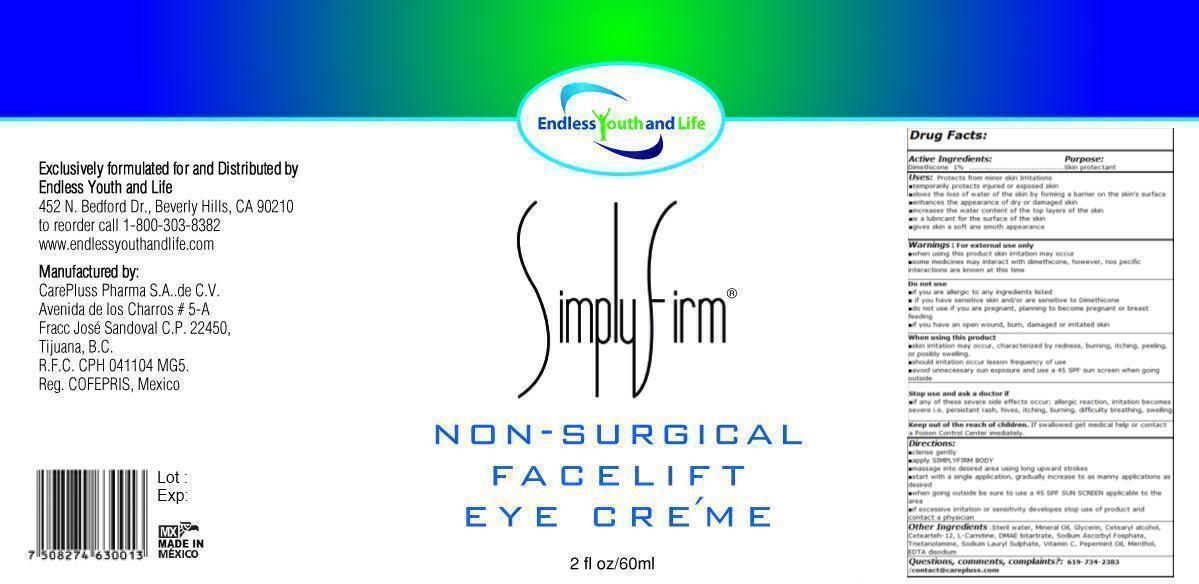 DRUG LABEL: Simply Firm Eye - Non-Surgical Face Lift
NDC: 51439-001 | Form: GEL
Manufacturer: CarePluss Pharma S.A. de C.V.
Category: otc | Type: HUMAN OTC DRUG LABEL
Date: 20130423

ACTIVE INGREDIENTS: DIMETHICONE 0.6 mg/60 mg
INACTIVE INGREDIENTS: WATER; ALMOND OIL; GLYCERIN; CETYL ALCOHOL; CETEARETH-12; MINERAL OIL; LEVOCARNITINE; DEANOL; SODIUM ASCORBYL PHOSPHATE; GREEN TEA LEAF; COFFEE BEAN; TROLAMINE; SODIUM DODECYLBENZENESULFONATE; ASCORBIC ACID; PEPPERMINT OIL; MINT; ALMOND; COCONUT; LIME (CITRUS); EDETIC ACID; METHYLPARABEN; PROPYLPARABEN; BUTYLATED HYDROXYTOLUENE; BUTYLATED HYDROXYANISOLE; SUNFLOWER OIL; VITIS VINIFERA SEED; POMEGRANATE SEED OIL; CARBOMER HOMOPOLYMER TYPE A (ALLYL PENTAERYTHRITOL CROSSLINKED)

Active Ingredient Purpose

Dimethicone 1% ........ skin protectant

PURPOSE

Uses: protects from minor skin irritations.

- temporarily protects injured or exposed skin
- slows the loss of water of the skin by forming a barrier on the skin's surface
- enhances the appearance of dry or damaged skin
- increases the water content of the top layers of the skin
- is a lubricant for the surface of the skin
- gives skin a soft and smooth appearance

Warnings: For external use only

- when using this product skin irritation may occur
- some medicines may interact with dimethicone, however, no specific interactions are known at this time

Do not use

- if you are allergic to any ingredients listed
- if you have sensitive skin and/or are sensitive to Dimethicone
- do not use if you are pregnant, planning to become pregnant, or breast feeding
- if you have an open wound, burn, damaged or irritaed skin

When using this product

- skin irritation may occur, characterized by redness, burning, itching, peeling, or possibly swelling
- should irritation occur lesson frequency of use
- avoid unnecessary sun exposure and use a 45 SPF sun screen when going outside

Stop use and ask a doctor

- if any of these severe side effects occur: allergic reaction, irritation become severe i.e. persistant rash, hives, itching, burning, difficulty breathing, swelling

Keep out of reach of children. If swallowed, get medical help or contact a Poison Control Center immediately.

Directions:

- cleanse gently
- apply SIMPLY FIRM BODY
- massage into desired area using long upward strokes
- start with a single application, gradually increase to as many applications as desired
- when going outside be sure to use a 45 SPF SUN SCREEN applicable to the area
- if excessive irritation or sensitivity develops stop use of product and contact a physician

INACTIVE INGREDIENT

Other ingredients: Water, Almond Oil, Glycerin, Cetearyl alcohol, Cetearteh-12, Mineral Oil, L-Carnitine, DMAE bitartrate, Sodium Ascorbyl Fosphate, Carbomer, Green Tea extract, Coffe Berry extract, Trietanolamine, Sodium Lauryl Sulphate, Vitamin C, Pepermint Oil, Menthol, Almond scent, Green Tea scent, Coco scent, EDTA disodium.

DOSAGE AND ADMINISTRATION

2 fl oz / 60 mL